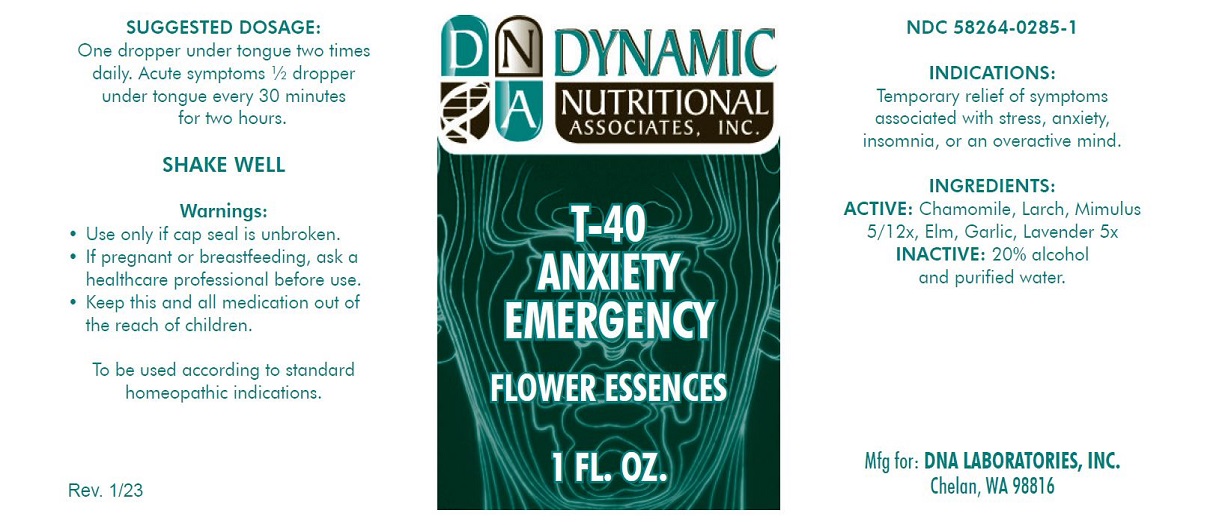 DRUG LABEL: T-40
NDC: 58264-0285 | Form: SOLUTION
Manufacturer: DNA Labs, Inc.
Category: homeopathic | Type: HUMAN OTC DRUG LABEL
Date: 20250109

ACTIVE INGREDIENTS: MATRICARIA CHAMOMILLA FLOWERING TOP 5 [hp_X]/1 mL; LARIX DECIDUA FLOWERING TOP 5 [hp_X]/1 mL; MIMULUS GUTTATUS FLOWERING TOP 5 [hp_X]/1 mL; LAVANDULA ANGUSTIFOLIA SUBSP. ANGUSTIFOLIA FLOWER 5 [hp_X]/1 mL; ELM 5 [hp_X]/1 mL; GARLIC 5 [hp_X]/1 mL
INACTIVE INGREDIENTS: ALCOHOL; WATER

T-40

NDC 58264-0285-1

INDICATIONS

PURPOSE

Temporary relief of symptoms associated with stress, anxiety, insomnia, or an overactive mind.

INGREDIENTS

ACTIVE

Chamomile 5X, 12X, Larch 5X, 12X, Mimulus 5X, 12X, Lavender 5X, Elm 5X, Garlic 5X

INACTIVE

20% alcohol and purified water.

SUGGESTED DOSAGE

One dropper under tongue two times daily. Acute symptoms ½ dropper under tongue every 30 minutes for two hours.

STORAGE AND HANDLING

SHAKE WELL

Warnings

- Use only if cap seal is unbroken.

PREGNANCY OR BREAST FEEDING

- If pregnant or breastfeeding, ask a healthcare professional before use.

KEEP OUT OF REACH OF CHILDREN

- Keep this and all medications out of the reach of children.

To be used according to standard homeopathic indications.

PRINCIPAL DISPLAY PANEL - 1 FL. OZ. Bottle Label

DYNAMIC
NUTRITIONAL
ASSOCIATES, INC.

T-40

ANXIETY

EMERGENCY

FLOWER ESSENCES

1 FL. OZ.